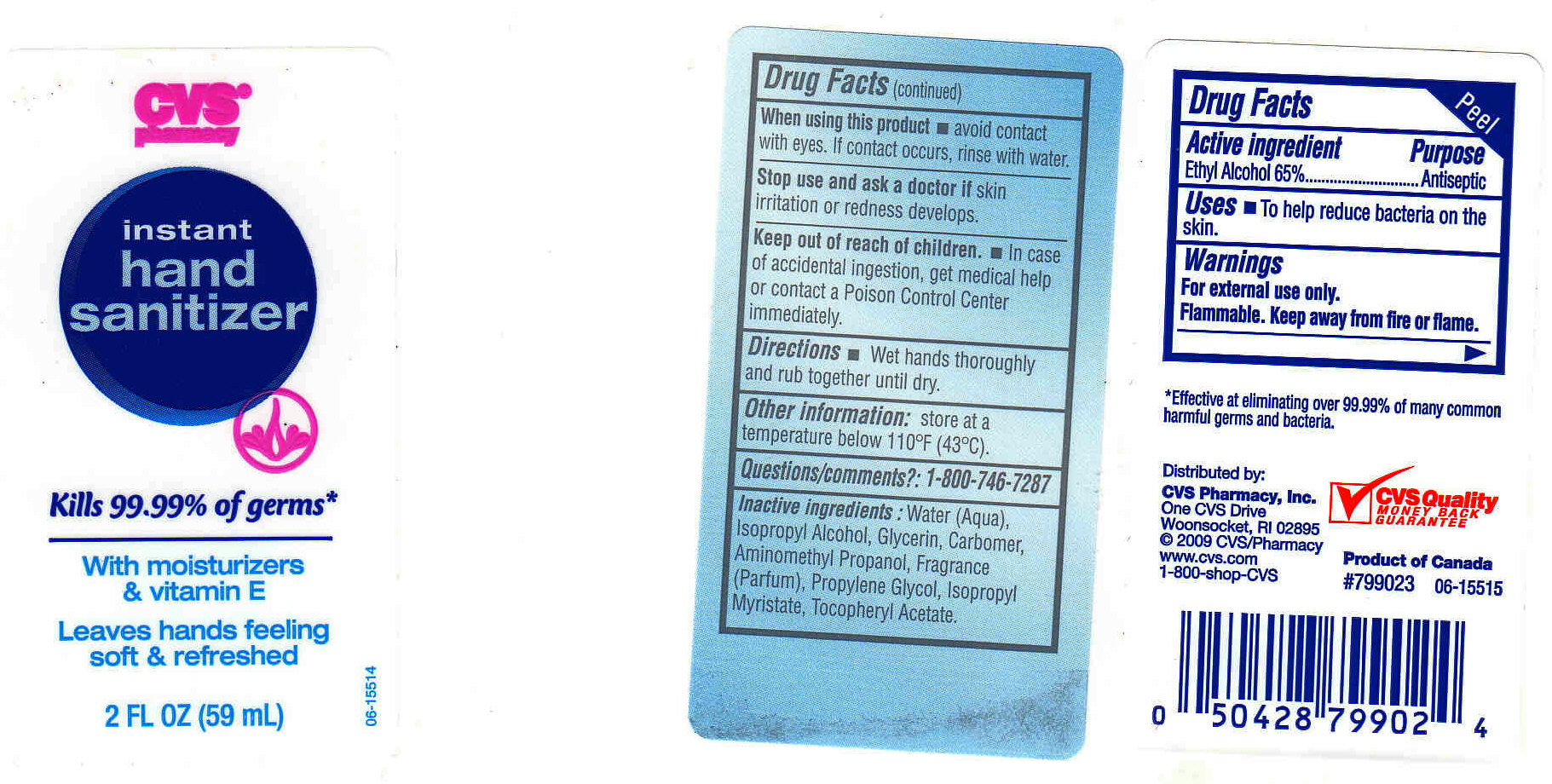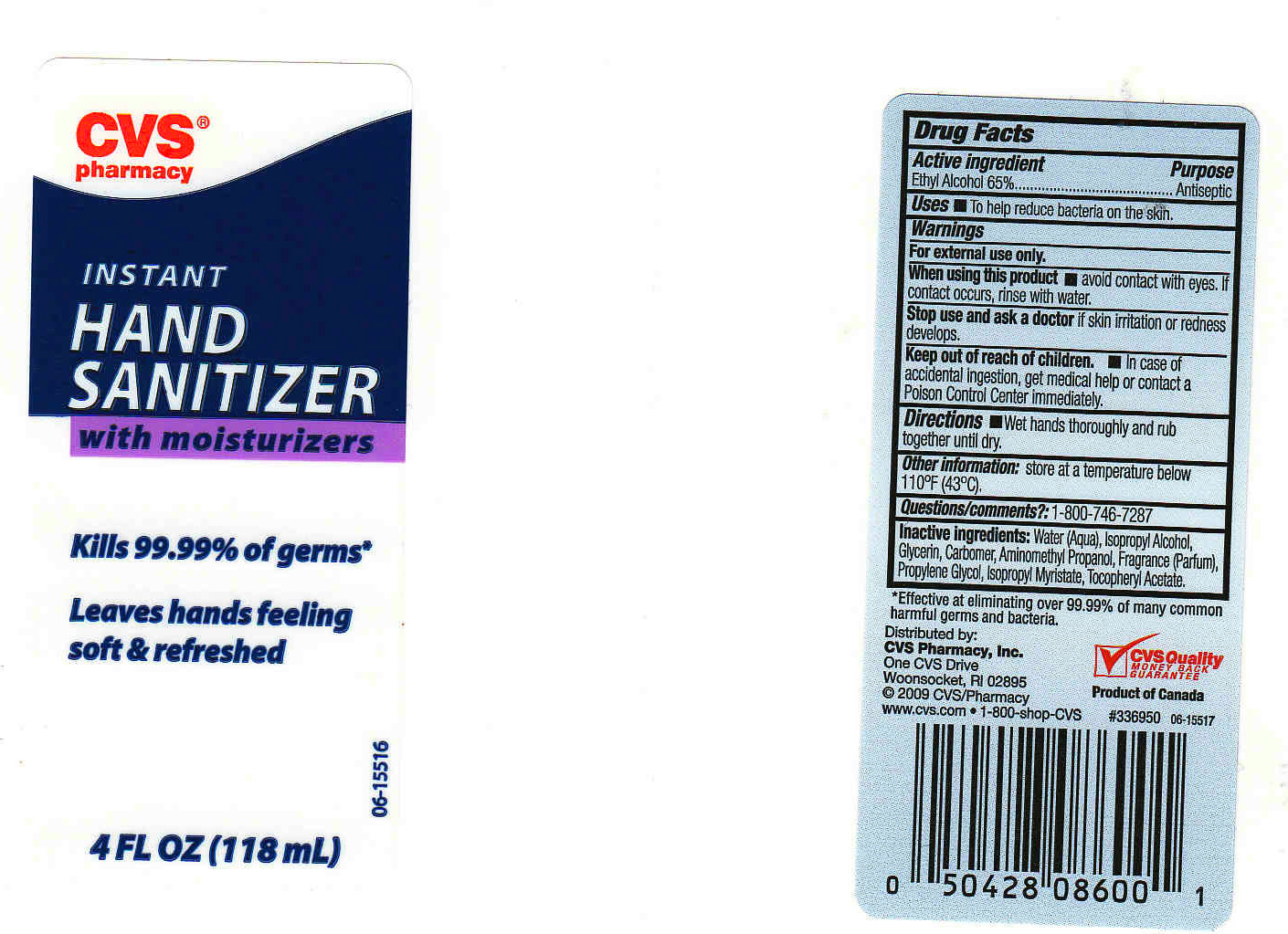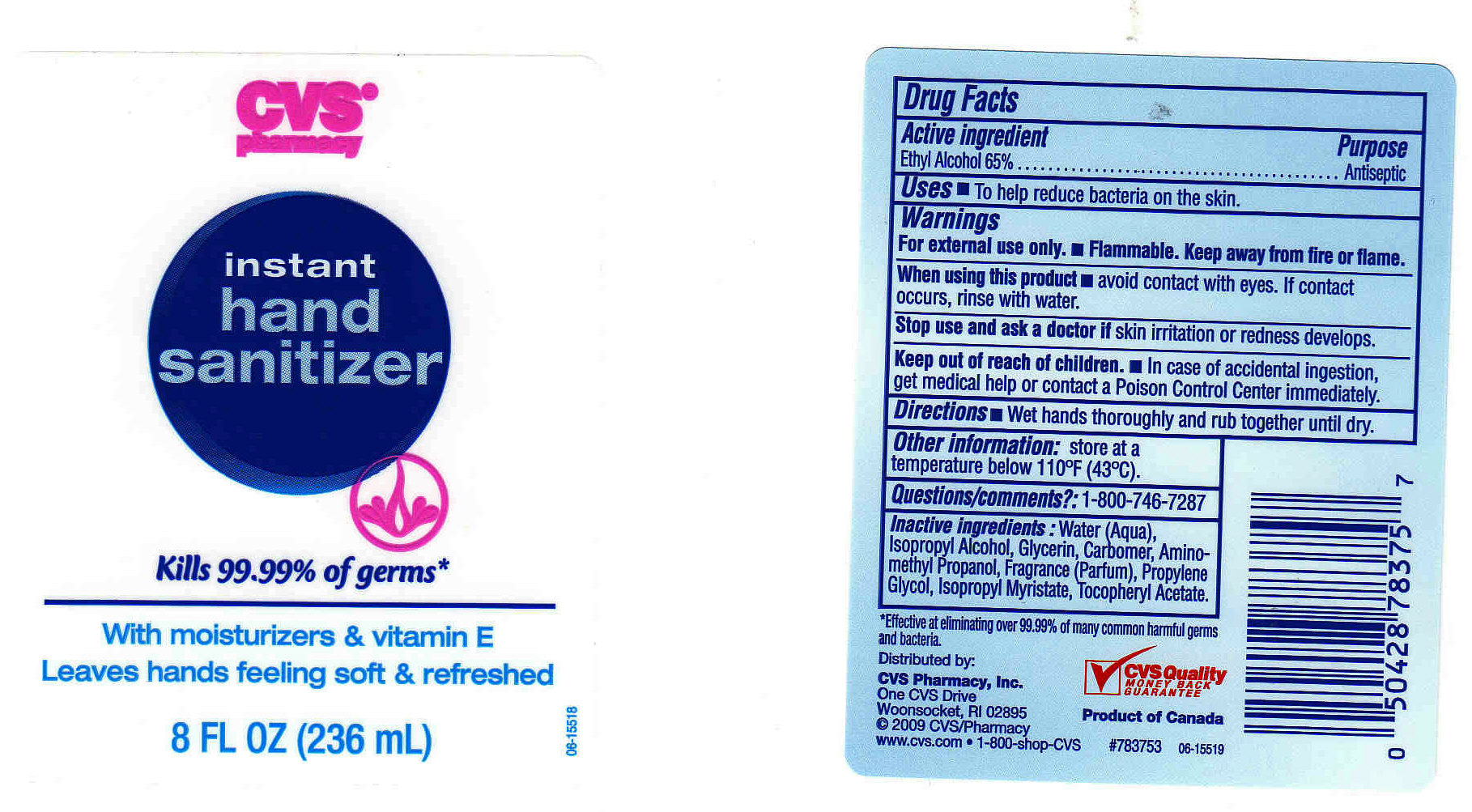 DRUG LABEL: CVS PHARMACY 
NDC: 63148-253 | Form: GEL
Manufacturer: Apollo Health and Beauty Care
Category: otc | Type: HUMAN OTC DRUG LABEL
Date: 20091010

ACTIVE INGREDIENTS: ALCOHOL 65.0000 mL/100 mL
INACTIVE INGREDIENTS: WATER 33.5700 mL/100 mL; ISOPROPYL ALCOHOL 0.5000 mL/100 mL; GLYCERIN 0.3000 mL/100 mL; CARBOMER HOMOPOLYMER TYPE C 0.2600 mL/100 mL; 2-AMINO-2-METHYL-1-PROPANOL 0.1600 mL/100 mL; PROPYLENE GLYCOL 0.1000 mL/100 mL; ISOPROPYL MYRISTATE 0.1000 mL/100 mL; ALPHA-TOCOPHEROL ACETATE 0.0100 mL/100 mL

CVS PHARMACY HAND SANITIZER WITH MOISTURIZERS AND VITAMIN E

ACTIVE INGREDIENT

ETHYL ALCOHOL 65% (ANTISEPTIC)

USES

TO HELP REDUCE BACTERIA ON THE SKIN

WARNINGS

- FOR EXTERNAL USE ONLY.
- FLAMMABLE. KEEP AWAY FROM FIRE OR FLAME.

WHEN USING THIS PRODUCT

AVOID CONTACT WITH EYES. IF CONTACT OCCURS, RINSE WITH WATER.

STOP USE AND ASK A DOCTOR IF

SKIN IRRITATION OR REDNESS DEVELOPS.

KEEP OUT OF REACH OF CHILDREN

IN CASE OF ACCIDENTAL INGESTION, GET MEDICAL HELP OR CONTACT A POISON CONTROL CENTER IMMEDIATELY.

QUESTIONS/COMMENTS?:

1-800-746-7287

OTHER INFORMATION

STORE AT A TEMPERATURE BELOW 110^0F (43^0C).

PACKAGE FRONT AND BACK LABELS

1. MM1: 2OZ (Labels2.jpg)
2. MM2: 4OZ (Labels4.jpg)
3. MM3: 8OZ (Labels8.jpg)